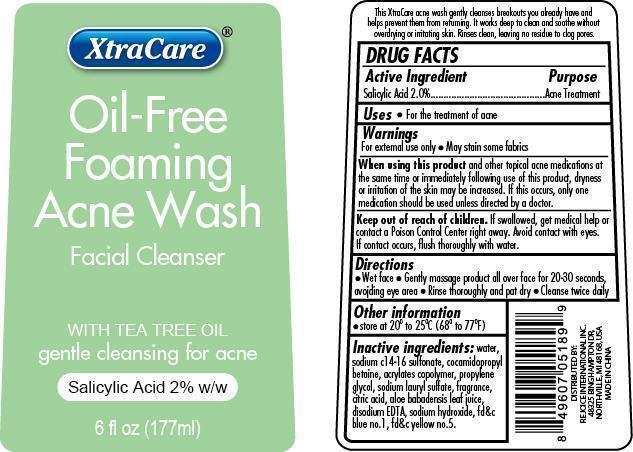 DRUG LABEL: Oil-Free Foaming Acne Wash Facial Cleanser
NDC: 57337-034 | Form: GEL
Manufacturer: Rejoice International
Category: otc | Type: HUMAN OTC DRUG LABEL
Date: 20240228

ACTIVE INGREDIENTS: SALICYLIC ACID 4 mg/177 mg
INACTIVE INGREDIENTS: WATER; SODIUM C14-16 OLEFIN SULFONATE; COCAMIDOPROPYL BETAINE; CARBOMER COPOLYMER TYPE A (ALLYL PENTAERYTHRITOL CROSSLINKED); PROPYLENE GLYCOL; SODIUM LAURYL SULFATE; CITRIC ACID MONOHYDRATE; ALOE VERA LEAF; EDETATE DISODIUM; SODIUM HYDROXIDE; FD&C BLUE NO. 1; FD&C YELLOW NO. 5

Oil-Free Foaming Acne Wash Facial Cleanser

Active Ingredient Purpose

Salicylic Acid 2.0% .......................... Acne Treatment

PURPOSE

XtraCare Oil-Free Foaming Acne Wash Facial Cleanser

WITH TEA TREE OIL

gentle cleansing for acne

Salicylic Acid 2% w/w

6 fl oz (177ml)

Keep out of reach of children. If swallowed, get medical help or contact a Poison Control Center right away. Avoid contact with eyes. If contact occurs, flush thoroughly with water.

INDICATIONS AND USAGE

This XtraCare acne wash gently cleanses breakouts you already have and helps prevent them from returning. It works deep to clean and soothe without overdrying or irritating skin. Rinses clean, leaving no residue to clog pores.

Warnings

For external use only. May stain some fabrics.

When using this product and other topical acne medications at the same time or immediately following use of this product, dryness or irritation of the skin may be increased. If this occurs, only one medication should be used unless directed by a doctor.

INACTIVE INGREDIENT

Inactive Ingredients: water, sodium c14-16 sulfonate, cocamidopropyl betaine, acrylates copolymer, propylene glycol, sodium lauryl sulfate, fragrance, citric acid, aloe barbadensis leaf juice, disodium EDTA, sodium hydroxide, fd&c blue no. 1, fd&c yellow no. 5

Other information:

store at 20o to 25oC (68o to 77oF)

DISTRIBUTED BY

REJOICE INTERNATIONAL INC

48235 BINGHAMPTON DR

NORTHVILLE, MI 48168 USA

MADE IN CHINA